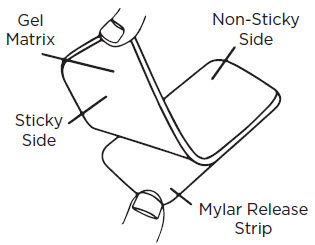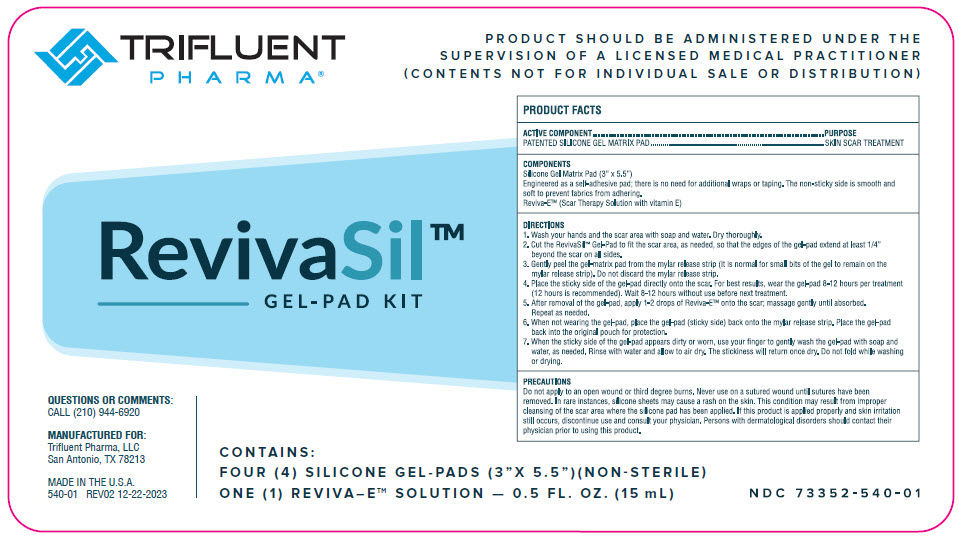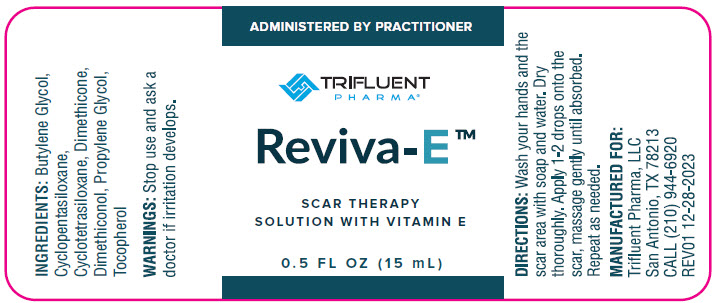 DRUG LABEL: Reviva-Sil
NDC: 73352-540 | Form: KIT | Route: TOPICAL
Manufacturer: Trifluent Pharma LLC
Category: other | Type: MEDICAL DEVICE
Date: 20240207

ACTIVE INGREDIENTS: DIMETHICONE 12 h/1 1
INACTIVE INGREDIENTS: DIMETHICONE 100; CYCLOMETHICONE 5; CYCLOMETHICONE 4; DIMETHICONOL (40 CST); TOCOPHEROL; BUTYLENE GLYCOL; PROPYLENE GLYCOL

REVIVASIL™ GEL- PAD KIT

USES

RevivaSil™ Gel-Pad Kit is intended for managing hypertrophic, hyperpigmented, and keloid scar tissue.

HOW SUPPLIED

Non-sterile product is labeled as such and supplied in protective packaging and container.

POSSIBLE REACTIONS INCLUDE

- Superficial maceration of the skin
- Skin discoloration
- Pruritus
- Rash

Rashes may occur on skin under gel-pad due to poor hygiene. Rashes may also result from wrapping gel-pad too tightly around skin. Stop use and ask a doctor if gel-pad is applied properly and skin irritation still occurs.

Discoloration of skin covered by gel-pad may temporarily occur in patients with darker complexions.

Do not use creams, lotions, sun block, or other silicone products on your skin when wearing gel-pad. Only apply gel-pad to clean, bare skin.

PRECAUTIONS

Do not apply to open wounds or third degree burns. Never use on a sutured wound until sutures have been removed or when any dermatological conditions disrupt the skin (such as a rash or burn). In rare instances, silicone sheets may cause a rash on the skin. This condition may result from improper cleansing of the scar area where the gel-pad has been applied. Stop use and ask a doctor if product is applied properly and skin irritation still occurs. Persons with dermatological disorders should contact their doctor prior to using this product.

DIRECTIONS FOR USE

1) Wash your hands and the scar area with soap and water. Dry thoroughly.
2) Cut the RevivaSil™ Gel-Pad to fit the scar area as needed, so that the edges extend at least 1/4" beyond the scar on all sides.
3) Gently peel the gel-pad from the Mylar release strip (it is normal for small bits of the gel to remain on the Mylar release strip). Do not discard the Mylar release strip.
4) Place the sticky side of the gel-pad directly onto the scar. For best results, wear the gel-pad 8-12 hours per treatment (12 hours is recommended). Wait 8-12 hours without use before next treatment.
5) After removal of the gel-pad, apply 1-2 drops of Reviva-E™ onto the scar; massage gently until absorbed. Repeat as needed.
6) When not wearing the gel-pad, place the gel-pad (sticky side) back onto the Mylar release strip. Place the gel-pad back into the original pouch for protection.
7) When the sticky side of the gel-pad appears dirty or worn, use your finger to gently wash the gel-pad with soap and water, as needed. Rinse with water and allow to air dry. The stickiness will return once dry. Do not fold while washing or drying.

* Proper use, and gentle care of the gel-pad will be re-usable up to eight (8) days.

PRODUCT FACTS

DESCRIPTION

Active Component | Purpose
Patented Silicone Gel Matrix Pad | Skin Scar Treatment

COMPONENTS

Silicone Gel Matrix Pad (3'' X 5.5'')

Engineered as a self-adhesive pad; there is no need for additional wraps or taping. The non-sticky side is smooth and soft to prevent fabrics from adhering.

DIRECTIONS

1) Wash your hands and the scar area with soap and water. Dry thoroughly.
2) Cut the RevivaSil™ Gel-Pad to fit the scar area as needed, so that the edges extend at least 1/4" beyond the scar on all sides.
3) Gently peel the gel-pad from the Mylar release strip (it is normal for small bits of the gel to remain on the Mylar release strip). Do not discard the Mylar release strip.
4) Place the sticky side of the gel-pad directly onto the scar. For best results, wear the gel-pad 8-12 hours per treatment (12 hours is recommended). Wait 8-12 hours without use before next treatment.
5) After removal of the gel-pad, apply 1-2 drops of Reviva-E™ onto the scar; massage gently until absorbed. Repeat as needed.
6) When not wearing the gel-pad, place the gel-pad (sticky side) back onto the Mylar release strip. Place the gel-pad back into the original pouch for protection.
7) When the sticky side of the gel-pad appears dirty or worn, use your finger to gently wash the gel-pad with soap and water, as needed. Rinse with water and allow to air dry. The stickiness will return once dry. Do not fold while washing or drying.

PRECAUTIONS

Do not apply to open wounds or third degree burns. Never use on a sutured wound until sutures have been removed or when any dermatological conditions disrupt the skin (such as a rash or burn). In rare instances, silicone sheets may cause a rash on the skin. This condition may result from improper cleansing of the scar area where the gel-pad has been applied. Stop use and ask a doctor if product is applied properly and skin irritation still occurs. Persons with dermatological disorders should contact their doctor prior to using this product.

PRINCIPAL DISPLAY PANEL - Kit Label

TRIFLUENT
PHARMA®

RevivaSil™
GEL-PAD KIT

QUESTIONS OR COMMENTS:
CALL (210) 944-6920

MANUFACTURED FOR:
Trifluent Pharma, LLC
San Antonio, TX 78213

MADE IN THE U.S.A.
540-01 REV02 12-22-2023

CONTAINS:
FOUR (4) SILICONE GEL-PADS (3" X 5.5") (NON-STERILE)
ONE (1) REVIVA-E™ SOLUTION – 0.5 FL. OZ. (15 mL)

PRODUCT SHOULD BE ADMINISTERED UNDER THE
SUPERVISION OF A LICENSED MEDICAL PRACTITIONER
(CONTENTS NOT FOR INDIVIDUAL SALE OR DISTRIBUTION)

NDC 73352-540-01

PRINCIPAL DISPLAY PANEL - 15 mL Bottle Label

ADMINISTERED BY PRACTITIONER

TRIFLUENT
PHARMA®

Reviva-E™

SCAR THERAPY
SOLUTION WITH VITAMIN E

0.5 FL OZ (15 mL)